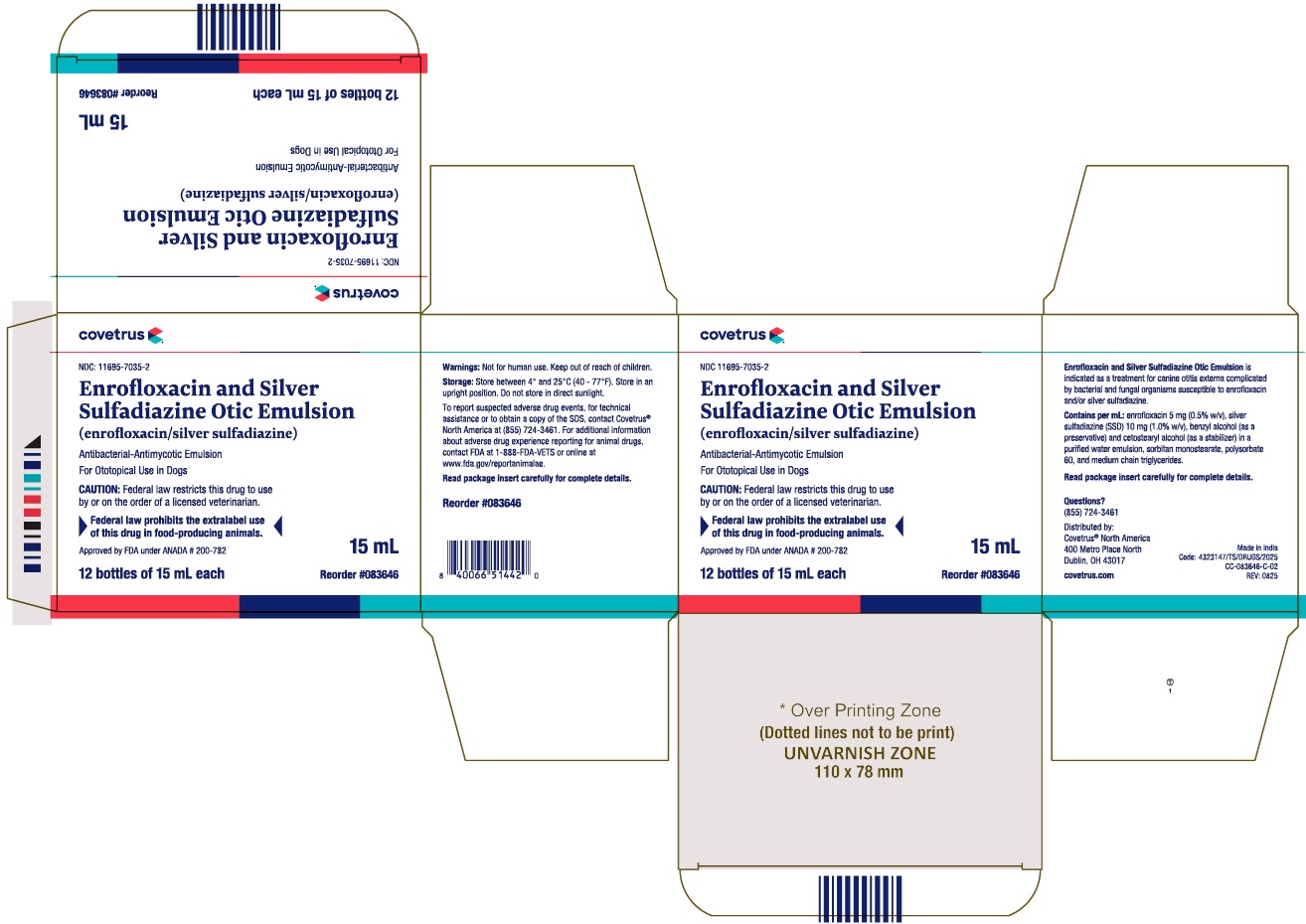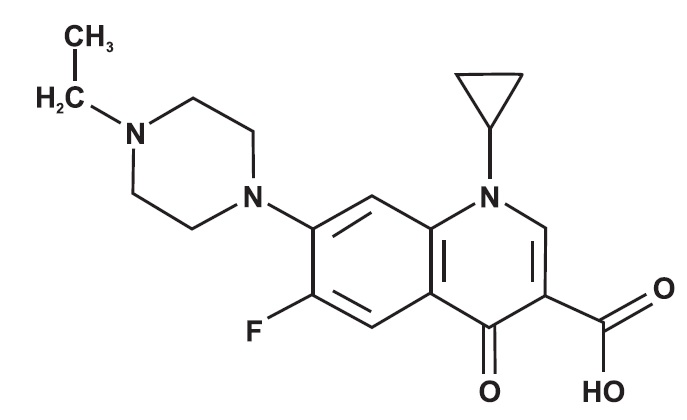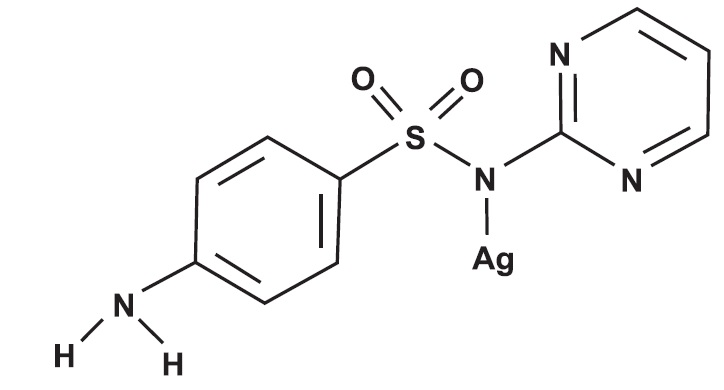 DRUG LABEL: Enrofloxacin and Silver Sulfadiazine Otic Emulsion
NDC: 11695-7035 | Form: EMULSION
Manufacturer: Covetrus
Category: animal | Type: PRESCRIPTION ANIMAL DRUG LABEL
Date: 20260107

ACTIVE INGREDIENTS: ENROFLOXACIN 5 mg/1 mL; SILVER SULFADIAZINE 10 mg/1 mL

Enrofloxacin and Silver Sulfadiazine Otic Emulsion
(enrofloxacin/silver sulfadiazine)
Antibacterial-Antimycotic Emulsion

For Ototopical Use In Dogs

Caution: Federal Law restricts this drug to use by or on the order of a licensed veterinarian.

►Federal law prohibits the extralabel use of this drug in food-producing animals.◄

PRODUCT DESCRIPTION:

Each milliliter of Enrofloxacin and Silver Sulfadiazine Otic Emulsion contains: enrofloxacin 5 mg (0.5% w/v), silver sulfadiazine (SSD) 10 mg (1.0% w/v), benzyl alcohol (as a preservative) and cetostearyl alcohol (as a stabilizer) in a purified water emulsion, sorbitan monostearate, polysorbate 60, and medium chain triglycerides. The active ingredients are delivered via a physiological carrier (a nonirritating emulsion).

CHEMICAL NOMENCLATURE AND STRUCTURE:

Enrofloxacin

1-Cyclopropyl-7-(4-ethyl-1-piperazinyl)-6-fluoro-1, 4-dihydro-4-oxo-3-quinolinecarboxylic acid.

Silver Sulfadiazine

Benzenesulfonamide, 4-amino-N-2-pyrimidinyl-monosilver

ACTIONS:

Enrofloxacin, a 4-fluoroquinolone compound, is bactericidal with activity against a broad spectrum of both Gram negative and Gram positive bacteria. Fluoroquinolones elicit their bactericidal activities through interactions with two intracellular enzymes, DNA gyrase (DNA topoisomerase II) and DNA topoisomerase IV, which are essential for bacterial DNA transcription, synthesis and replication. It is believed that fluoroquinolones actively bind with bacterial DNA:ENZYME complexes and thereby inhibit the essential processes catalyzed by the enzymes (DNA supercoiling and chromosomal decatenation).^1 The ultimate outcome of the fluoroquinolone intervention is DNA fragmentation and bacterial cell death.^2,3

Silver sulfadiazine (SSD) is synthesized from silver nitrate and sodium sulfadiazine.^4 This compound has a wide spectrum of antimicrobial activity against Gram negative and Gram positive bacteria and is also an effective antimycotic.^5,6 SSD suppresses microbial growth through inhibition of DNA replication and modification of the cell membrane.

MICROBIOLOGY:

In clinical field trials, enrofloxacin/silver sulfadiazine otic demonstrated elimination or reduction of clinical signs associated with otitis externa and in vitro activity against cultured organisms. enrofloxacin/silver sulfadiazine otic is effective when used as a treatment for canine otitis externa associated with one or more of the following organisms: Malassezia pachydermatis, coagulase-positive Staphylococcus spp., Pseudomonas aeruginosa, Enterobacter spp., Proteus mirabilis, Streptococci spp., Aeromonas hydrophila, Aspergillus spp., Klebsiella pneumoniae, and Candida albicans.

In vitro assays, such as disk-diffusion and agar/broth-dilution, are used to determine the susceptibilities of microbes to antimicrobial therapies. Results of agar/broth-dilution assays are reported as a Minimal Inhibitory Concentration (MIC) which represents the lowest antimicrobial concentration, expressed in μg/mL, capable of inhibiting the growth of a pathogenic microorganism. MICs are used in conjunction with pharmacokinetics to predict the in vivo efficacy of systemically administered antimicrobials. Topical administration of enrofloxacin/silver sulfadiazine otic to an exudate and debris-free canal, however, will generally result in local antimicrobial concentrations that greatly exceed serum and tissue levels resulting from systemic therapy. Therefore, when using enrofloxacin/silver sulfadiazine otic as a treatment for canine otitis externa, interpret susceptibility data cautiously.

INDICATIONS:

Enrofloxacin and Silver Sulfadiazine Otic Emulsion is indicated as a treatment for canine otitis externa complicated by bacterial and fungal organisms susceptible to enrofloxacin and/or silver sulfadiazine (see Microbiology section).

EFFECTIVENESS:

Due to its combination of active ingredients, enrofloxacin/silver sulfadiazine otic provides antimicrobial therapy against bacteria and fungi (which includes yeast) commonly encountered in cases of canine otitis externa.

The effectiveness of enrofloxacin/silver sulfadiazine otic was evaluated in a controlled, double-blind, multi-site clinical trial. One hundred and sixty-nine dogs (n=169), with naturally occurring active otitis externa participated in the study. The presence of active disease was verified by aural cytology, microbial culture and otoscopy/clinical scoring. Qualified cases were randomly assigned to either enrofloxacin/silver sulfadiazine otic treatment (n=113) or to a comparable placebo-based regimen (n=56). Treatments were administered twice daily for up to 14 days. Assessment of effectiveness was based on continued resolution of clinical signs 3 to 4 days following administration of the last dose.

At study conclusion, enrofloxacin/silver sulfadiazine otic was found to be a significantly more effective treatment for canine otitis externa than the placebo regimen. Based on the scoring system used to assess treatment response, therapeutic success occurred in 67% of enrofloxacin/silver sulfadiazine otic-treated infections compared to 14% with placebo (r-value^2 0.001) after 14 days of treatment.

CONTRAINDICATIONS:

Enrofloxacin and Silver Sulfadiazine Otic Emulsion is contraindicated in dogs with suspected or known hypersensitivity to quinolones and/or sulfonamides.

HUMAN WARNINGS:

Not for human use. Keep out of the reach of children. Avoid contact with eyes. In case of contact, immediately flush eyes with copious amounts of water for 15 minutes. In case of dermal contact, wash skin with soap and water. Consult a physician if irritation develops or persists following ocular or dermal exposures. Individuals with a history of hypersensitivity to quinolone compounds or antibacterials should avoid handling this product. In humans, there is a risk of user photosensitization within a few hours after excessive exposure to quinolones. If excessive accidental exposure occurs, avoid direct sunlight.

PRECAUTIONS:

The use of Enrofloxacin and Silver Sulfadiazine Otic Emulsion in dogs with perforated tympanic membranes has not been evaluated. Therefore, the integrity of the tympanic membrane should be evaluated before administering this product. If hearing or vestibular dysfunction is noted during the course of treatment, discontinue use of Enrofloxacin and Silver Sulfadiazine Otic Emulsion.

Quinolone-class drugs should be used with caution in animals with known or suspected Central Nervous System (CNS) disorders. In such animals, quinolones have, in rare instances, been associated with CNS stimulation which may lead to convulsive seizures.

Quinolone-class drugs have been associated with cartilage erosions in weightbearing joints and other forms of arthropathy in immature animals of various species.

The safe use of Enrofloxacin and Silver Sulfadiazine Otic Emulsion in dogs used for breeding purposes, during pregnancy, or in lactating bitches, has not been evaluated.

ADVERSE REACTIONS:

During clinical trials, 2 of 113 (1.7%) dogs exhibited reactions that may have resulted from treatment with enrofloxacin/silver sulfadiazine otic. Both cases displayed local hypersensitivity responses of the aural epithelium to some component within the enrofloxacin/silver sulfadiazine otic formulation. The reactions were characterized by acute inflammation of the ear canal and pinna.

To report suspected adverse drug events, for technical assistance or to obtain a copy of the SDS, contact Covetrus® North America at (855) 724-3461. For additional information about adverse drug experience reporting for animal drugs, contact FDA at 1-888-FDA-VETS or online at www.fda.gov/reportanimalae.

SAFETY:

General Safety Study:

In a target animal safety study, enrofloxacin/silver sulfadiazine otic was administered in both ears of 24 clinically normal beagle dogs at either recommended or exaggerated dosages: 10, 30 or 50 drops applied twice daily for 42 consecutive days. A control group of 8 beagle dogs was treated by administering 50 drops of vehicle in one ear twice daily for 42 consecutive days, with the contralateral ear untreated. Erythema was noted in all groups, including both treated and untreated ears in the controls, which resolved following termination of treatment.

Oral Safety Study:

In order to test safety in case of ingestion, enrofloxacin/silver sulfadiazine otic was administered, twice daily for 14 consecutive days, to the dorsum of the tongue and to the left buccal mucosa of 6 clinically normal dogs. No adverse local or systemic reactions were reported.

DOSAGE AND ADMINISTRATION:

Shake well before each use.

Tilt head so that the affected ear is presented in an upward orientation. Administer a sufficient quantity of Enrofloxacin and Silver Sulfadiazine Otic Emulsion to coat the aural lesions and the external auditory canal.

As a general guide, administer 5-10 drops per treatment in dogs weighing 35 lbs. or less and 10-15 drops per treatment in dogs weighing more than 35 lbs. Following treatment, gently massage the ear so as to ensure complete and uniform distribution of the medication throughout the external ear canal. Apply twice daily for a duration of up to 14 days.

STORAGE:

Store between 4° and 25°C (40 - 77°F). Store in an upright position. Do not store in direct sunlight.

HOW SUPPLIED:

Enrofloxacin and Silver Sulfadiazine Otic Emulsion (enrofloxacin/silver sulfadiazine)

Size Presentation

15 mL White LDPE bottle with HDPE cap and dropper

REFERENCES:

1. Hooper DC and Wolfson JS. Mechanisms of quinolone action and bacterial killing in quinolone antimicrobial agents. Washington DC, American Society for Microbiology, 2nd ed., 1993: 53-75.

2. Gootz TD and Brightly KE. Fluoroquinolone antibacterial: mechanism of action, resistance and clinical aspects. Medicinal Research Reviews 1996:16 (5): 433-486.

3. Drlica K and Zhoa X. DNA gyrase, topoisomerase IV and the 4-quinolones. Microbiology and Molecular Biology Reviews 1997: 61(3): 377-392.

4. Fox CL. Silver sulfadiazine: a new topical therapy for Pseudomonas in burns. Archives of Surgery 1968: 96:184-188.

5. Wlodkowski TJ and Rosenkranz HS. Antifungal activity of silver sulfadiazine. Lancet 1973: 2:739-740.

6. Schmidt A. In vitro activity of climbazole, clotrimazole and silver sulfadiazine against isolates of Malassezia pachy-dermatis. J of Vet Medicine Series B 1997: 44:193-197.

Approved by FDA under ANADA # 200-782

Questions?

(855) 724-3461

Distributed by:
Covetrus North America
400 Metro Place North
Dublin, OH 43017
covetrus.com

Made in India
REV: 0825

© 2024 Covetrus, Inc. All rights reserved

PACKAGE LABEL.PRINCIPAL DISPLAY PANEL

NDC 11695-7035-2

Enrofloxacin and Silver Sulfadiazine Otic Emulsion

(enrofloxacin/silver sulfadiazine)

Antibacterial-Antimycotic Emulsion

For Ototopical Use in dogs

CAUTION: Federal law restricts this drug to use by or on the order of a veterinarian.

►Federal law prohibits the extralabel use of this drug in food-producing animals.◄

Approved by FDA under ANADA # 200-782

15 mL

12 bottles of 15 mL each

Reorder #083646